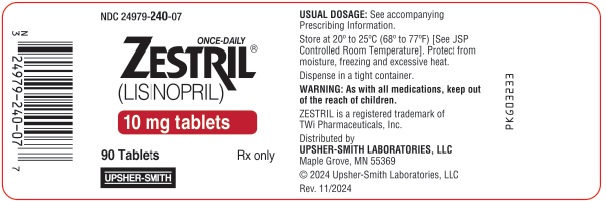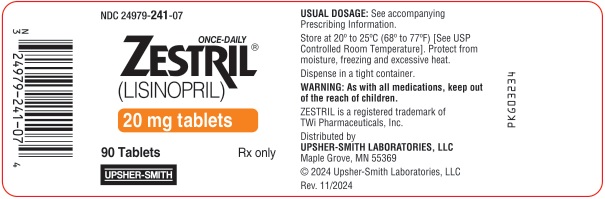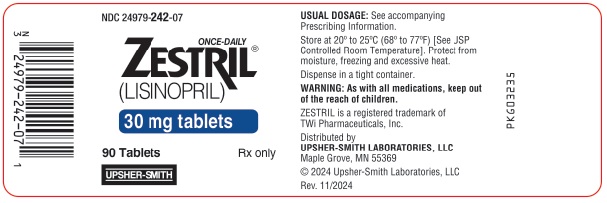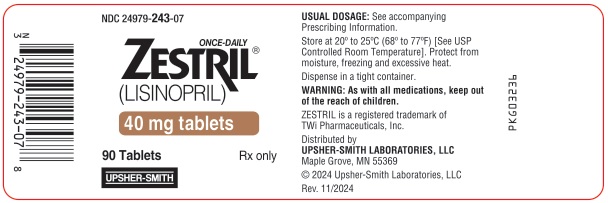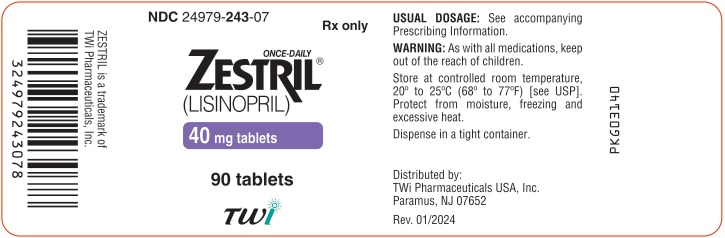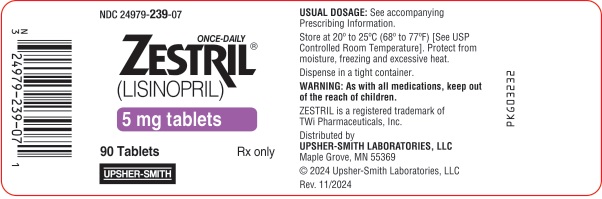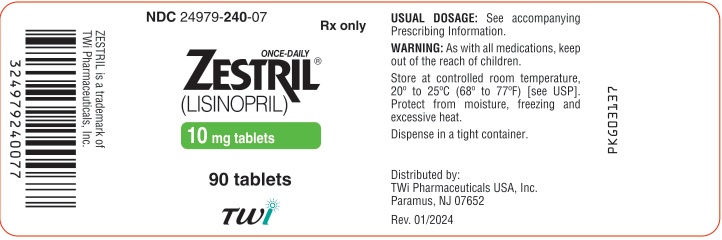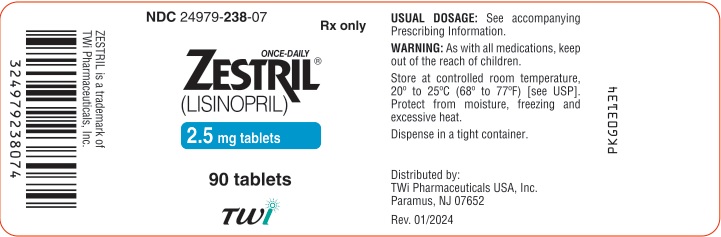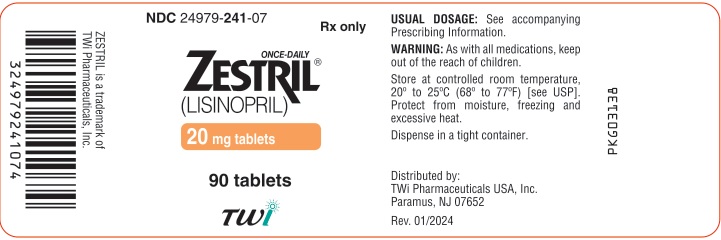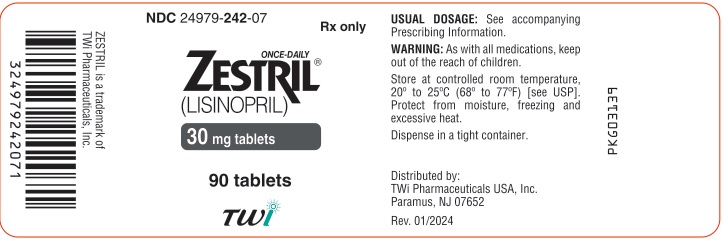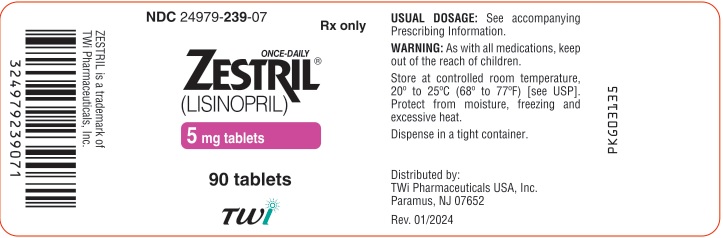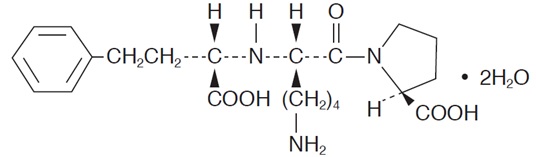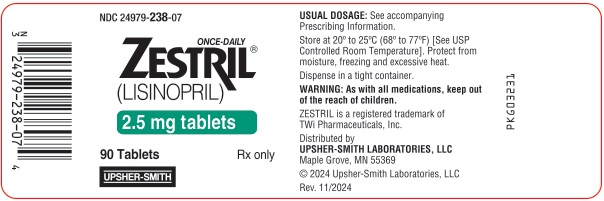 DRUG LABEL: Zestril
NDC: 24979-238 | Form: TABLET
Manufacturer: Upsher-Smith Laboratories, LLC
Category: prescription | Type: HUMAN PRESCRIPTION DRUG LABEL
Date: 20250102

ACTIVE INGREDIENTS: LISINOPRIL 2.5 mg/1 1
INACTIVE INGREDIENTS: DIBASIC CALCIUM PHOSPHATE DIHYDRATE; MAGNESIUM STEARATE; MANNITOL; STARCH, CORN

HIGHLIGHTS OF PRESCRIBING INFORMATION

These highlights do not include all the information needed to use ZESTRIL safely and effectively. See full prescribing information for ZESTRIL
ZESTRIL® (lisinopril) tablets, for oral use
Initial U.S. Approval: 1988

WARNING: FETAL TOXICITY

See full prescribing information for complete boxed warning.

- When pregnancy is detected, discontinue Zestril as soon as possible. (5.1)
- Drugs that act directly on the renin-angiotensin system can cause injury and death to the developing fetus. (5.1)

1 INDICATIONS AND USAGE

Zestril is an angiotensin converting enzyme (ACE) inhibitor indicated for:

- Treatment of hypertension in adults and pediatric patients 6 years of age and older (1.1)
- Adjunct therapy for heart failure (1.2)
- Treatment of Acute Myocardial Infarction (1.3)

2 DOSAGE AND ADMINISTRATION

- Hypertension: Initial adult dose is 10 mg once daily. Titrate up to 40 mg daily based on blood pressure response. Initiate patients on diuretics at 5 mg once daily (2.1)
- Pediatric patients with glomerular filtration rate > 30 mL/min/1.73m^2: Initial dose in patients 6 years of age and older is 0.07 mg per kg (up to 5 mg total) once daily (2.1)
- Heart Failure: Initiate with 5 mg once daily. Increase dose as tolerated to 40 mg daily (2.2)
- Acute Myocardial Infarction (MI): Give 5 mg within 24 hours of MI. Followed by 5 mg after 24 hours, then 10 mg once daily (2.3)
- Renal Impairment: For patients with creatinine clearance ≥ 10 mL/min and ≤ 30 mL/min, halve usual initial dose. For patients with creatinine clearance < 10 mL/min or on hemodialysis, the recommended initial dose is 2.5 mg (2.4)

3 DOSAGE FORMS AND STRENGTHS

Tablets: 2.5 mg, 5 mg, 10 mg, 20 mg, 30 mg, 40 mg (3)

4 CONTRAINDICATIONS

- Angioedema or a history of hereditary or idiopathic angioedema (4)
- Hypersensitivity (4)
- Co-administration of aliskiren with Zestril in patients with diabetes (4, 7.4)

5 WARNINGS AND PRECAUTIONS

- Angioedema: Discontinue Zestril, provide appropriate therapy and monitor until resolved (5.2)
- Renal impairment: Monitor renal function periodically (5.3)
- Hypotension: Patients with other heart or renal diseases have increased risk, monitor blood pressure after initiation (5.4)
- Hyperkalemia: Monitor serum potassium periodically (5.5)
- Cholestatic jaundice and hepatic failure: Monitor for jaundice or signs of liver failure (5.6)

6 ADVERSE REACTIONS

Common adverse reactions (events 2% greater than placebo) by use:

- Hypertension: headache, dizziness and cough (6.1)
- Heart Failure: hypotension and chest pain (6.1)
- Acute Myocardial Infarction: hypotension (6.1)

To report SUSPECTED ADVERSE REACTIONS, contact Upsher-Smith Laboratories, LLC at 1-855-899-9180 or FDA at 1-800-FDA-1088 or www.fda.gov/medwatch.

7 DRUG INTERACTIONS

- Diuretics: Excessive drop in blood pressure (7.1)
- NSAIDS: Increased risk of renal impairment and loss of antihypertensive efficacy (7.3)
- Dual inhibition of the renin-angiotensin system: Increased risk of renal impairment, hypotension and hyperkalemia (7.4)
- Lithium: Symptoms of lithium toxicity (7.5)
- Gold: Nitritoid reactions have been reported (7.6)
- Concomitant mTOR inhibitor or neprilysin inhibitor use may increase angioedema risk (7.7, 7.8)

8 USE IN SPECIFIC POPULATIONS

- Lactation: Advise not to breastfeed. (8.2)
- Race: Less antihypertensive effect in blacks than non blacks (8.6)

FULL PRESCRIBING INFORMATION

WARNING: FETAL TOXICITY

- When pregnancy is detected, discontinue ZESTRIL as soon as possible [see Warnings and Precautions (5.1)].
- Drugs that act directly on the renin-angiotensin system can cause injury and death to the developing fetus [see Warnings and Precautions (5.1)].

1 INDICATIONS AND USAGE

1.1 Hypertension

Zestril is indicated for the treatment of hypertension in adult patients and pediatric patients 6 years of age and older to lower blood pressure. Lowering blood pressure lowers the risk of fatal and non-fatal cardiovascular events, primarily strokes and myocardial infarctions. These benefits have been seen in controlled trials of antihypertensive drugs from a wide variety of pharmacologic classes.

Control of high blood pressure should be part of comprehensive cardiovascular risk management, including, as appropriate, lipid control, diabetes management, antithrombotic therapy, smoking cessation, exercise, and limited sodium intake. Many patients will require more than 1 drug to achieve blood pressure goals. For specific advice on goals and management, see published guidelines, such as those of the National High Blood Pressure Education Program’s Joint National Committee on Prevention, Detection, Evaluation, and Treatment of High Blood Pressure (JNC).

Numerous antihypertensive drugs, from a variety of pharmacologic classes and with different mechanisms of action, have been shown in randomized controlled trials to reduce cardiovascular morbidity and mortality, and it can be concluded that it is blood pressure reduction, and not some other pharmacologic property of the drugs, that is largely responsible for those benefits. The largest and most consistent cardiovascular outcome benefit has been a reduction in the risk of stroke, but reductions in myocardial infarction and cardiovascular mortality also have been seen regularly.

Elevated systolic or diastolic pressure causes increased cardiovascular risk, and the absolute risk increase per mmHg is greater at higher blood pressures, so that even modest reductions of severe hypertension can provide substantial benefit. Relative risk reduction from blood pressure reduction is similar across populations with varying absolute risk, so the absolute benefit is greater in patients who are at higher risk independent of their hypertension (for example, patients with diabetes or hyperlipidemia), and such patients would be expected to benefit from more aggressive treatment to a lower blood pressure goal.

Some antihypertensive drugs have smaller blood pressure effects (as monotherapy) in black patients, and many antihypertensive drugs have additional approved indications and effects (e.g., on angina, heart failure, or diabetic kidney disease). These considerations may guide selection of therapy.

Zestril may be administered alone or with other antihypertensive agents [see Clinical Studies (14.1) ].

1.2 Heart Failure

Zestril is indicated to reduce signs and symptoms of systolic heart failure [see Clinical Studies (14.2) ].

1.3 Reduction of Mortality in Acute Myocardial Infarction

Zestril is indicated for the reduction of mortality in treatment of hemodynamically stable patients within 24 hours of acute myocardial infarction. Patients should receive, as appropriate, the standard recommended treatments such as thrombolytics, aspirin and beta-blockers [see Clinical Studies (14.3) ].

2 DOSAGE AND ADMINISTRATION

2.1 Hypertension

Initial Therapy in adults: The recommended initial dose is 10 mg once a day. Dosage should be adjusted according to blood pressure response. The usual dosage range is 20 mg to 40 mg per day administered in a single daily dose. Doses up to 80 mg have been used but do not appear to give greater effect.

Use with diuretics in adults

If blood pressure is not controlled with Zestril alone, a low dose of a diuretic may be added (e.g., hydrochlorothiazide, 12.5 mg). After the addition of a diuretic, it may be possible to reduce the dose of Zestril.

The recommended starting dose in adult patients with hypertension taking diuretics is 5 mg once per day.

Pediatric Patients 6 years of age and older with hypertension

For pediatric patients with glomerular filtration rate > 30 mL/min/1.73m^2, the recommended starting dose is 0.07 mg per kg once daily (up to 5 mg total). Dosage should be adjusted according to blood pressure response up to a maximum of 0.61 mg per kg (up to 40 mg) once daily. Doses above 0.61 mg per kg (or in excess of 40 mg) have not been studied in pediatric patients [see Clinical Pharmacology (12.3) ].

Zestril is not recommended in pediatric patients < 6 years or in pediatric patients with glomerular filtration rate < 30 mL/min/1.73m^2 [see Use in Specific Populations (8.4) and Clinical Studies (14.1) ].

2.2 Heart Failure

The recommended starting dose for Zestril, when used with diuretics and (usually) digitalis as adjunctive therapy for systolic heart failure, is 5 mg once daily. The recommended starting dose in these patients with hyponatremia (serum sodium < 130 mEq/L) is 2.5 mg once daily. Increase as tolerated to a maximum of 40 mg once daily.

Diuretic dose may need to be adjusted to help minimize hypovolemia, which may contribute to hypotension [see Warnings and Precautions (5.4), and Drug Interactions (7.1) ]. The appearance of hypotension after the initial dose of Zestril does not preclude subsequent careful dose titration with the drug, following effective management of the hypotension.

2.3 Reduction of Mortality in Acute Myocardial Infarction

In hemodynamically stable patients within 24 hours of the onset of symptoms of acute myocardial infarction, give Zestril 5 mg orally, followed by 5 mg after 24 hours, 10 mg after 48 hours and then 10 mg once daily. Dosing should continue for at least six weeks.

Initiate therapy with 2.5 mg in patients with a low systolic blood pressure (≤ 120 mmHg and > 100 mmHg) during the first 3 days after the infarct [see Warnings and Precautions (5.4) ]. If hypotension occurs (systolic blood pressure ≤ 100 mmHg) a daily maintenance dose of 5 mg may be given with temporary reductions to 2.5 mg if needed. If prolonged hypotension occurs (systolic blood pressure < 90 mmHg for more than 1 hour) Zestril should be withdrawn.

2.4 Dose in Patients with Renal Impairment

No dose adjustment of Zestril is required in patients with creatinine clearance > 30 mL/min. In patients with creatinine clearance ≥ 10 mL/min and ≤ 30 mL/min, reduce the initial dose of Zestril to half of the usual recommended dose i.e., hypertension, 5 mg; systolic heart failure, 2.5 mg and acute MI, 2.5 mg. Up titrate as tolerated to a maximum of 40 mg daily. For patients on hemodialysis or creatinine clearance < 10 mL/min, the recommended initial dose is 2.5 mg once daily [see Use in Specific Populations (8.7) and Clinical Pharmacology (12.3)].

3 DOSAGE FORMS AND STRENGTHS

2.5 mg are white, round, biconvex, uncoated tablets identified as “ZESTRIL 2 1/2” on one side and “135” on the other side.
5 mg are pink, capsule-shaped, biconvex, bisected, uncoated tablets identified as “ZESTRIL” on one side and “130” on the other side.
10 mg are pink, round, biconvex, uncoated tablets identified as “ZESTRIL 10” on one side and “131” on the other side.
20 mg are pale brownish red, round, biconvex, uncoated tablets identified as “ZESTRIL 20” on one side and “132” on the other side.
30 mg are pale brownish red, round, biconvex, uncoated tablets identified as “ZESTRIL 30” on one side and “133” on the other side.
40 mg are yellow, round, biconvex, uncoated tablets identified as “ZESTRIL 40” on one side and “134” on the other side.

4 CONTRAINDICATIONS

Zestril is contraindicated in combination with a neprilysin inhibitor (e.g., sacubitril). Do not administer Zestril within 36 hours of switching to or from sacubitril/valsartan, a neprilysin inhibitor [see Warnings and Precautions (5.2)].

Zestril is contraindicated in patients with:

- a history of angioedema or hypersensitivity related to previous treatment with an angiotensin converting enzyme inhibitor
- hereditary or idiopathic angioedema

Do not co-administer aliskiren with ZESTRIL in patients with diabetes [see Drug Interactions (7.4)].

5 WARNINGS AND PRECAUTIONS

5.1 Fetal Toxicity

Zestril can cause fetal harm when administered to a pregnant woman. Use of drugs that act on the renin-angiotensin system during the second and third trimesters of pregnancy reduces fetal renal function and increases fetal and neonatal morbidity and death. Resulting oligohydramnios can be associated with fetal lung hypoplasia and skeletal deformations. Potential neonatal adverse effects include skull hypoplasia, anuria, hypotension, renal failure, and death. When pregnancy is detected, discontinue Zestril as soon as possible [see Use in specific Populations (8.1) ].

5.2 Angioedema and Anaphylactoid Reactions

Patients taking concomitant mTOR inhibitor (e.g. temsirolimus, sirolimus, everolimus) therapy or a neprilysin inhibitor may be at increased risk for angioedema. [see Drug Interactions (7.7, 7.8)].

Angioedema

Head and Neck Angioedema

Angioedema of the face, extremities, lips, tongue, glottis and/or larynx, including some fatal reactions, have occurred in patients treated with angiotensin converting enzyme inhibitors, including Zestril, at any time during treatment. Patients with involvement of the tongue, glottis or larynx are likely to experience airway obstruction, especially those with a history of airway surgery. Zestril should be promptly discontinued and appropriate therapy and monitoring should be provided until complete and sustained resolution of signs and symptoms of angioedema has occurred.

Patients with a history of angioedema unrelated to ACE inhibitor therapy may be at increased risk of angioedema while receiving an ACE inhibitor [see Contraindications (4) ]. ACE inhibitors have been associated with a higher rate of angioedema in black than in non-black patients.

Intestinal Angioedema

Intestinal angioedema has occurred in patients treated with ACE inhibitors. These patients presented with abdominal pain (with or without nausea or vomiting); in some cases there was no prior history of facial angioedema and C-1 esterase levels were normal. In some cases, the angioedema was diagnosed by procedures including abdominal CT scan or ultrasound, or at surgery, and symptoms resolved after stopping the ACE inhibitor.

Anaphylactoid Reactions

Anaphylactoid Reactions During Desensitization

Two patients undergoing desensitizing treatment with hymenoptera venom while receiving ACE inhibitors sustained life- threatening anaphylactoid reactions.

Anaphylactoid Reactions During Dialysis

Sudden and potentially life threatening anaphylactoid reactions have occurred in some patients dialyzed with high-flux membranes and treated concomitantly with an ACE inhibitor. In such patients, dialysis must be stopped immediately, and aggressive therapy for anaphylactoid reactions must be initiated. Symptoms have not been relieved by antihistamines in these situations. In these patients, consideration should be given to using a different type of dialysis membrane or a different class of antihypertensive agent. Anaphylactoid reactions have also been reported in patients undergoing low-density lipoprotein apheresis with dextran sulfate absorption.

5.3 Impaired Renal Function

Monitor renal function periodically in patients treated with Zestril. Changes in renal function including acute renal failure can be caused by drugs that inhibit the renin-angiotensin system. Patients whose renal function may depend in part on the activity of the renin-angiotensin system (e.g., patients with renal artery stenosis, chronic kidney disease, severe congestive heart failure, post-myocardial infarction or volume depletion) may be at particular risk of developing acute renal failure on Zestril. Consider withholding or discontinuing therapy in patients who develop a clinically significant decrease in renal function on Zestril [see Adverse Reactions (6.1) , Drug Interactions (7.4) ].

5.4 Hypotension

Zestril can cause symptomatic hypotension, sometimes complicated by oliguria, progressive azotemia, acute renal failure or death. Patients at risk of excessive hypotension include those with the following conditions or characteristics: heart failure with systolic blood pressure below 100 mmHg, ischemic heart disease, cerebrovascular disease, hyponatremia, high dose diuretic therapy, renal dialysis, or severe volume and/or salt depletion of any etiology.

In these patients, Zestril should be started under very close medical supervision and such patients should be followed closely for the first two weeks of treatment and whenever the dose of Zestril and/or diuretic is increased. Avoid use of Zestril in patients who are hemodynamically unstable after acute MI.

Symptomatic hypotension is also possible in patients with severe aortic stenosis or hypertrophic cardiomyopathy.

Surgery/Anesthesia

In patients undergoing major surgery or during anesthesia with agents that produce hypotension, Zestril may block angiotensin II formation secondary to compensatory renin release. If hypotension occurs and is considered to be due to this mechanism, it can be corrected by volume expansion.

5.5 Hyperkalemia

Serum potassium should be monitored periodically in patients receiving Zestril. Drugs that inhibit the renin angiotensin system can cause hyperkalemia. Risk factors for the development of hyperkalemia include renal insufficiency, diabetes mellitus, and the concomitant use of potassium-sparing diuretics, potassium supplements and/or potassium-containing salt substitutes [see Drug Interactions (7.1) ].

5.6 Hepatic Failure

ACE inhibitors have been associated with a syndrome that starts with cholestatic jaundice or hepatitis and progresses to fulminant hepatic necrosis and sometimes death. The mechanism of this syndrome is not understood. Patients receiving ACE inhibitors who develop jaundice or marked elevations of hepatic enzymes should discontinue the ACE inhibitor and receive appropriate medical treatment.

6 ADVERSE REACTIONS

6.1 Clinical Trials Experience

Because clinical trials are conducted under widely varying conditions, adverse reaction rates observed in the clinical studies of a drug cannot be directly compared to rates in the clinical studies of another drug and may not reflect the rates observed in practice.

Hypertension

In clinical trials in patients with hypertension treated with Zestril, 5.7% of patients on Zestril discontinued with adverse reactions.

The following adverse reactions (events 2% greater on Zestril than on placebo) were observed with Zestril alone: headache (by 3.8%), dizziness (by 3.5%), cough (by 2.5%).

Heart Failure

In patients with systolic heart failure treated with Zestril for up to four years, 11% discontinued therapy with adverse reactions. In controlled studies in patients with heart failure, therapy was discontinued in 8.1% of patients treated with Zestril for 12 weeks, compared to 7.7% of patients treated with placebo for 12 weeks.

The following adverse reactions (events 2% greater on Zestril than on placebo) were observed with Zestril: hypotension (by 3.8%), chest pain (by 2.1%).

In the two-dose ATLAS trial [see Clinical Studies (14.2) ] in heart failure patients, withdrawals due to adverse reactions were not different between the low and high groups, either in total number of discontinuation (17% to 18%) or in rare specific reactions (< 1%). The following adverse reactions, mostly related to ACE inhibition, were reported more commonly in the high dose group:

Table 1 Dose-related Adverse Drug Reactions: ATLAS trial

 | High Dose (n=1568) | Low Dose (n=1596)
Dizziness | 19% | 12%
Hypotension | 11% | 7%
Creatinine increased | 10% | 7%
Hyperkalemia | 6% | 4%
Syncope | 7% | 5%

Acute Myocardial Infarction

Patients treated with Zestril had a higher incidence of hypotension (by 5.3%) and renal dysfunction (by 1.3%) compared with patients not taking Zestril.

Other clinical adverse reactions occurring in 1% or higher of patients with hypertension or heart failure treated with Zestril in controlled clinical trials and do not appear in other sections of labeling are listed below:

Body as a whole: Fatigue, asthenia, orthostatic effects.

Digestive: Pancreatitis, constipation, flatulence, dry mouth, diarrhea.

Hematologic: Rare cases of bone marrow depression, hemolytic anemia, leukopenia/neutropenia and thrombocytopenia.

Endocrine: Diabetes mellitus, inappropriate antidiuretic hormone secretion.

Metabolic: Gout.

Skin: Urticaria, alopecia, photosensitivity, erythema, flushing, diaphoresis, cutaneous pseudolymphoma, toxic epidermal necrolysis, Stevens - Johnson syndrome, and pruritus.

Special Senses: Visual loss, diplopia, blurred vision, tinnitus, photophobia, taste disturbances, olfactory disturbance.

Urogenital: Impotence.

Miscellaneous: A symptom complex has been reported which may include a positive ANA, an elevated erythrocyte sedimentation rate, arthralgia/arthritis, myalgia, fever, vasculitis, eosinophilia, leukocytosis, paresthesia and vertigo. Rash, photosensitivity or other dermatological manifestations may occur alone or in combination with these symptoms.

Clinical Laboratory Test Findings

Serum Potassium: In clinical trials hyperkalemia (serum potassium greater than 5.7 mEq/L) occurred in 2.2% and 4.8% of Zestril-treated patients with hypertension and heart failure, respectively [see Warnings and Precautions (5.5) ].

Creatinine, Blood Urea Nitrogen: Minor increases in blood urea nitrogen and serum creatinine, reversible upon discontinuation of therapy, were observed in about 2% of patients with hypertension treated with Zestril alone. Increases were more common in patients receiving concomitant diuretics and in patients with renal artery stenosis [see Warnings and Precautions (5.4) ]. Reversible minor increases in blood urea nitrogen and serum creatinine were observed in 11.6% of patients with heart failure on concomitant diuretic therapy. Frequently, these abnormalities resolved when the dosage of the diuretic was decreased.

Patients with acute myocardial infarction in the GISSI-3 trial treated with Zestril had a higher (2.4% versus 1.1% in placebo) incidence of renal dysfunction in-hospital and at six weeks (increasing creatinine concentration to over 3 mg/dL or a doubling or more of the baseline serum creatinine concentration).

Hemoglobin and Hematocrit: Small decreases in hemoglobin and hematocrit (mean decreases of approximately 0.4 g% and 1.3 vol%, respectively) occurred frequently in patients treated with Zestril but were rarely of clinical importance in patients without some other cause of anemia. In clinical trials, less than 0.1% of patients discontinued therapy due to anemia.

6.2 Post-marketing Experience

The following adverse reactions have been identified during post-approval use of Zestril that are not included in other sections of labeling. Because these reactions are reported voluntarily from a population of uncertain size, it is not always possible to reliably estimate their frequency or establish a causal relationship to drug exposure.

Other reactions include:

Metabolism and nutrition disorders

Hyponatremia [see Warnings and Precautions (5.4) ], cases of hypoglycemia in diabetic patients on oral antidiabetic agents or insulin [see Drug Interactions (7.2) ].

Nervous system and psychiatric disorders

Mood alterations (including depressive symptoms), mental confusion, hallucinations

Skin and subcutaneous tissue disorders

Psoriasis

7 DRUG INTERACTIONS

7.1 Diuretics

Initiation of Zestril in patients on diuretics may result in excessive reduction of blood pressure. The possibility of hypotensive effects with Zestril can be minimized by either decreasing or discontinuing the diuretic or increasing the salt intake prior to initiation of treatment with Zestril. If this is not possible, reduce the starting dose of Zestril [see Dosage and Administration (2.2) and Warnings and Precautions (5.4)].

Zestril attenuates potassium loss caused by thiazide-type diuretics. Potassium-sparing diuretics (spironolactone, amiloride, triamterene, and others) can increase the risk of hyperkalemia. Therefore, if concomitant use of such agents is indicated, monitor the patient’s serum potassium frequently.

7.2 Antidiabetics

Concomitant administration of Zestril and antidiabetic medicines (insulins, oral hypoglycemic agents) may cause an increased blood-glucose-lowering effect with risk of hypoglycemia.

7.3 Non-Steroidal Anti-Inflammatory Agents Including Selective Cyclooxygenase-2 Inhibitors (COX-2 Inhibitors)

In patients who are elderly, volume-depleted (including those on diuretic therapy), or with compromised renal function, coadministration of NSAIDs, including selective COX-2 inhibitors, with ACE inhibitors, including lisinopril, may result in deterioration of renal function, including possible acute renal failure. These effects are usually reversible. Monitor renal function periodically in patients receiving lisinopril and NSAID therapy.

The antihypertensive effect of ACE inhibitors, including lisinopril, may be attenuated by NSAIDs.

7.4 Dual Blockade of the Renin-Angiotensin System (RAS)

Dual blockade of the RAS with angiotensin receptor blockers, ACE inhibitors, or aliskiren is associated with increased risks of hypotension, hyperkalemia, and changes in renal function (including acute renal failure) compared to monotherapy.

The VA NEPHRON trial enrolled 1,448 patients with type 2 diabetes, elevated urinary-albumin-to-creatinine ratio, and decreased estimated glomerular filtration rate (GFR 30 mL/min to 89.9 mL/min), randomized them to lisinopril or placebo on a background of losartan therapy and followed them for a median of 2.2 years. Patients receiving the combination of losartan and lisinopril did not obtain any additional benefit compared to monotherapy for the combined endpoint of decline in GFR, end state renal disease, or death, but experienced an increased incidence of hyperkalemia and acute kidney injury compared with the monotherapy group.

In general, avoid combined use of RAS inhibitors. Closely monitor blood pressure, renal function and electrolytes in patients on Zestril and other agents that affect the RAS.

Do not co-administer aliskiren with Zestril in patients with diabetes. Avoid use of aliskiren with Zestril in patients with renal impairment (GFR <60 mL/min).

7.5 Lithium

Lithium toxicity has been reported in patients receiving lithium concomitantly with drugs, which cause elimination of sodium, including ACE inhibitors. Lithium toxicity was usually reversible upon discontinuation of lithium and the ACE inhibitor. Monitor serum lithium levels during concurrent use.

7.6 Gold

Nitritoid reactions (symptoms include facial flushing, nausea, vomiting and hypotension) have been reported rarely in patients on therapy with injectable gold (sodium aurothiomalate) and concomitant ACE inhibitor therapy including Zestril.

7.7 mTOR Inhibitors

Patients taking concomitant mTOR inhibitor (e.g. temsirolimus, sirolimus, everolimus) therapy may be at increased risk for angioedema. [see Warnings and Precautions (5.2) ]

7.8 Neprilysin Inhibitor

Patients taking concomitant neprilysin inhibitors may be at increased risk for angioedema. [see Warnings and Precautions (5.2)]

8 USE IN SPECIFIC POPULATIONS

8.1 Pregnancy

Risk Summary

Zestril can cause fetal harm when administered to a pregnant woman. Use of drugs that act on the renin-angiotensin system during the second and third trimesters of pregnancy reduces fetal renal function and increases fetal and neonatal morbidity and death. Most epidemiologic studies examining fetal abnormalities after exposure to antihypertensive use in the first trimester have not distinguished drugs affecting the renin-angiotensin system from other antihypertensive agents. When pregnancy is detected, discontinue Zestril as soon as possible.

The estimated background risk of major birth defects and miscarriage for the indicated population(s) are unknown. In the general U.S. population, the estimated background risk of major birth defects and miscarriage in clinically recognized pregnancies is 2% to 4% and 15% to 20%, respectively.

Clinical Considerations

Disease-associated maternal and/or embryo/fetal risk

Hypertension in pregnancy increases the maternal risk for pre-eclampsia, gestational diabetes, premature delivery, and delivery complications (e.g., need for cesarean section, and post-partum hemorrhage). Hypertension increases the fetal risk for intrauterine growth restriction and intrauterine death. Pregnant women with hypertension should be carefully monitored and managed accordingly.

Fetal/Neonatal Adverse Reactions

Oligohydramnios in pregnant women who use drugs affecting the renin-angiotensin system in the second and third trimesters of pregnancy can result in the following: reduced fetal renal function leading to anuria and renal failure, fetal lung hypoplasia and skeletal deformations, including skull hypoplasia, hypotension, and death. In the unusual case that there is no appropriate alternative to therapy with drugs affecting the renin-angiotensin system for a particular patient, apprise the mother of the potential risk to the fetus.

Perform serial ultrasound examinations to assess the intra-amniotic environment. Fetal testing may be appropriate, based on the week of pregnancy. Patients and physicians should be aware, however, that oligohydramnios may not appear until after the fetus has sustained irreversible injury. Closely observe infants with histories of in utero exposure to Zestril for hypotension, oliguria, and hyperkalemia. If oliguria or hypotension occur in neonates with a history of in utero exposure to Zestril, support blood pressure and renal perfusion. Exchange transfusions or dialysis may be required as a means of reversing hypotension and substituting for disordered renal function.

8.2 Lactation

Risk Summary

No data are available regarding the presence of lisinopril in human milk or the effects of lisinopril on the breastfed infant or on milk production. Lisinopril is present in rat milk. Because of the potential for severe adverse reactions in the breastfed infant, advise women not to breastfeed during treatment with Zestril.

8.4 Pediatric Use

Antihypertensive effects and safety of Zestril have been established in pediatric patients aged 6 to 16 years [see Dosage and Administration (2.1) and Clinical Studies (14.1)]. No relevant differences between the adverse reaction profile for pediatric patients and adult patients were identified.

Safety and effectiveness of Zestril have not been established in pediatric patients under the age 6 or in pediatric patients with glomerular filtration rate < 30 mL/min/1.73 m^2 [see Dosage and Administration (2.1), Clinical Pharmacology (12.3), and Clinical Studies (14.1)].

Neonates with a history of in utero exposure to Zestril

If oliguria or hypotension occurs, direct attention toward support of blood pressure and renal perfusion. Exchange transfusions or dialysis may be required as a means of reversing hypotension and/or substituting for disordered renal function.

8.5 Geriatric Use

No dosage adjustment with Zestril is necessary in elderly patients. In a clinical study of Zestril in patients with myocardial infarctions (GISSI-3 Trial) 4,413 (47%) were 65 and over, while 1,656 (18%) were 75 and over. In this study, 4.8 % of patients aged 75 years and older discontinued Zestril treatment because of renal dysfunction vs. 1.3% of patients younger than 75 years. No other differences in safety or effectiveness were observed between elderly and younger patients, but greater sensitivity of some older individuals cannot be ruled out.

8.6 Race

ACE inhibitors, including Zestril, have an effect on blood pressure that is less in black patients than in non blacks.

8.7 Renal Impairment

Dose adjustment of Zestril is required in patients undergoing hemodialysis or whose creatinine clearance is ≤ 30 mL/min. No dose adjustment of Zestril is required in patients with creatinine clearance > 30 mL/min [see Dosage and Administration (2.4) and Clinical Pharmacology (12.3)].

10 OVERDOSAGE

Following a single oral dose of 20 g/kg no lethality occurred in rats, and death occurred in one of 20 mice receiving the same dose. The most likely manifestation of overdosage would be hypotension, for which the usual treatment would be intravenous infusion of normal saline solution.

Lisinopril can be removed by hemodialysis [see Clinical Pharmacology (12.3)].

11 DESCRIPTION

Lisinopril is an oral long-acting angiotensin converting enzyme (ACE) inhibitor. Lisinopril, a synthetic peptide derivative, is chemically described as (S)-1-[N2-(1-carboxy-3-phenylpropyl)-L-lysyl]-L-proline dihydrate. Its empirical formula is C21H31N3O52H2O and its structural formula is:

Lisinopril is a white to off-white, crystalline powder, with a molecular weight of 441.53. It is soluble in water and sparingly soluble in methanol and practically insoluble in ethanol.

Zestril is supplied as 2.5 mg, 5 mg, 10 mg, 20 mg, 30 mg and 40 mg tablets for oral administration.

Inactive Ingredients:

2.5 mg tablets - calcium phosphate, magnesium stearate, mannitol, starch.

5 mg, 10 mg, 20 mg and 30 mg tablets - calcium phosphate, magnesium stearate, mannitol, red ferric oxide, starch.

40 mg tablets - calcium phosphate, magnesium stearate, mannitol, starch, yellow ferric oxide.

12 CLINICAL PHARMACOLOGY

12.1 Mechanism of Action

Lisinopril inhibits angiotensin-converting enzyme (ACE) in human subjects and animals. ACE is a peptidyl dipeptidase that catalyzes the conversion of angiotensin I to the vasoconstrictor substance, angiotensin II. Angiotensin II also stimulates aldosterone secretion by the adrenal cortex. The beneficial effects of lisinopril in hypertension and heart failure appear to result primarily from suppression of the renin-angiotensin-aldosterone system. Inhibition of ACE results in decreased plasma angiotensin II which leads to decreased vasopressor activity and to decreased aldosterone secretion. The latter decrease may result in a small increase of serum potassium. In hypertensive patients with normal renal function treated with Zestril alone for up to 24 weeks, the mean increase in serum potassium was approximately 0.1 mEq/L; however, approximately 15% of patients had increases greater than 0.5 mEq/L and approximately 6% had a decrease greater than 0.5 mEq/L. In the same study, patients treated with Zestril and hydrochlorothiazide for up to 24 weeks had a mean decrease in serum potassium of 0.1 mEq/L; approximately 4% of patients had increases greater than 0.5 mEq/L and approximately 12% had a decrease greater than 0.5 mEq/L [see Clinical Studies (14.1)]. Removal of angiotensin II negative feedback on renin secretion leads to increased plasma renin activity.

ACE is identical to kininase, an enzyme that degrades bradykinin. Whether increased levels of bradykinin, a potent vasodepressor peptide, play a role in the therapeutic effects of Zestril remains to be elucidated.

While the mechanism through which Zestril lowers blood pressure is believed to be primarily suppression of the renin-angiotensin-aldosterone system, Zestril is antihypertensive even in patients with low-renin hypertension. Although Zestril was antihypertensive in all races studied, Black hypertensive patients (usually a low-renin hypertensive population) had a smaller average response to monotherapy than non Black patients.

Concomitant administration of Zestril and hydrochlorothiazide further reduced blood pressure in Black and non-Black patients and any racial differences in blood pressure response were no longer evident.

12.2 Pharmacodynamics

Hypertension

Adult Patients: Administration of Zestril to patients with hypertension results in a reduction of both supine and standing blood pressure to about the same extent with no compensatory tachycardia. Symptomatic postural hypotension is usually not observed although it can occur and should be anticipated in volume and/or salt-depleted patients [see Warnings and Precautions (5.4)]. When given together with thiazide-type diuretics, the blood pressure lowering effects of the two drugs are approximately additive.

In most patients studied, onset of antihypertensive activity was seen at one hour after oral administration of an individual dose of Zestril, with peak reduction of blood pressure achieved by 6 hours. Although an antihypertensive effect was observed 24 hours after dosing with recommended single daily doses, the effect was more consistent and the mean effect was considerably larger in some studies with doses of 20 mg or more than with lower doses; however, at all doses studied, the mean antihypertensive effect was substantially smaller 24 hours after dosing than it was 6 hours after dosing.

The antihypertensive effects of Zestril are maintained during long-term therapy. Abrupt withdrawal of Zestril has not been associated with a rapid increase in blood pressure, or a significant increase in blood pressure compared to pretreatment levels.

Non-Steroidal Anti-Inflammatory Agents

In a study in 36 patients with mild to moderate hypertension where the antihypertensive effects of Zestril alone were compared to Zestril given concomitantly with indomethacin, the use of indomethacin was associated with a reduced effect, although the difference between the two regimens was not significant.

12.3 Pharmacokinetics

Adult Patients: Following oral administration of Zestril, peak serum concentrations of lisinopril occur within about 7 hours, although there was a trend to a small delay in time taken to reach peak serum concentrations in acute myocardial infarction patients. Food does not alter the bioavailability of Zestril. Declining serum concentrations exhibit a prolonged terminal phase, which does not contribute to drug accumulation. This terminal phase probably represents saturable binding to ACE and is not proportional to dose. Upon multiple dosing, lisinopril exhibits an effective half-life of 12 hours.

Lisinopril does not appear to be bound to other serum proteins. Lisinopril does not undergo metabolism and is excreted unchanged entirely in the urine. Based on urinary recovery, the mean extent of absorption of lisinopril is approximately 25%, with large intersubject variability (6% to 60%) at all doses tested (5mg to 80 mg). The absolute bioavailability of lisinopril is reduced to 16% in patients with stable NYHA Class II-IV congestive heart failure, and the volume of distribution appears to be slightly smaller than that in normal subjects. The oral bioavailability of lisinopril in patients with acute myocardial infarction is similar to that in healthy volunteers.

Impaired renal function decreases elimination of lisinopril, which is excreted principally through the kidneys, but this decrease becomes clinically important only when the glomerular filtration rate is below 30 mL/min. Above this glomerular filtration rate, the elimination half-life is little changed. With greater impairment, however, peak and trough lisinopril levels increase, time to peak concentration increases and time to attain steady state is prolonged [see Dosage and Administration (2.4) ]. Lisinopril can be removed by hemodialysis.

Pediatric Patients: The pharmacokinetics of lisinopril were studied in 29 pediatric hypertensive patients between 6 years and 16 years with glomerular filtration rate > 30 mL/min/1.73 m^2. After doses of 0.1 mg per kg to 0.2 mg per kg, steady state peak plasma concentrations of lisinopril occurred within 6 hours and the extent of absorption based on urinary recovery was about 28%. These values are similar to those obtained previously in adults. The typical value of lisinopril oral clearance (systemic clearance/absolute bioavailability) in a child weighing 30 kg is 10 L/h, which increases in proportion to renal function. In a multicenter, open-label pharmacokinetic study of daily oral lisinopril in 22 pediatric hypertensive patients with stable kidney transplant (ages 7 to 17 years; estimated glomerular filtration rate > 30 mL/min/1.73 m^2), dose normalized exposures were in the range reported previously in children without a kidney transplant.

13 NONCLINICAL TOXICOLOGY

13.1 Carcinogenesis, Mutagenesis, Impairment of Fertility

There was no evidence of a tumorigenic effect when lisinopril was administered for 105 weeks to male and female rats at doses up to 90 mg per kg per day (about 56 or 9 times [Calculations assume a human weight of 50 kg and human body surface area of 1.62m^2] the maximum recommended daily human dose, based on body weight and body surface area, respectively). There was no evidence of carcinogenicity when lisinopril was administered for 92 weeks to (male and female) mice at doses up to 135 mg per kg per day (about 84 times the maximum recommended daily human dose). This dose was 6.8 times the maximum human dose based on body surface area in mice.

Lisinopril was not mutagenic in the Ames microbial mutagen test with or without metabolic activation. It was also negative in a forward mutation assay using Chinese hamster lung cells. Lisinopril did not produce single strand DNA breaks in an in vitro alkaline elution rat hepatocyte assay. In addition, lisinopril did not produce increases in chromosomal aberrations in an in vitro test in Chinese hamster ovary cells or in an in vivo study in mouse bone marrow.

There were no adverse effects on reproductive performance in male and female rats treated with up to 300 mg per kg per day of lisinopril. This dose is 188 times and 30 times the maximum human dose when based on mg/kg and mg/m^2, respectively.

Studies in rats indicate that lisinopril crosses the blood brain barrier poorly. Multiple doses of lisinopril in rats do not result in accumulation in any tissues. Milk of lactating rats contains radioactivity following administration of ^14C lisinopril. By whole body autoradiography, radioactivity was found in the placenta following administration of labeled drug to pregnant rats, but none was found in the fetuses.

14 CLINICAL STUDIES

14.1 Hypertension

Two dose-response studies utilizing a once-daily regimen were conducted in 438 mild to moderate hypertensive patients not on a diuretic. Blood pressure was measured 24 hours after dosing. An antihypertensive effect of Zestril was seen with 5 mg of Zestril in some patients. However, in both studies blood pressure reduction occurred sooner and was greater in patients treated with 10 mg, 20 mg or 80 mg of Zestril than patients treated with 5 mg of Zestril.

In controlled clinical studies of patients with mild to moderate hypertension, patients were treated with Zestril 20 mg to 80 mg daily, hydrochlorothiazide 12.5 mg to 50 mg daily or atenolol 50 mg to 200 mg daily; and in other studies of patients with moderate to severe hypertension, patients were treated with Zestril 20 mg to 80 mg daily or metoprolol 100 mg to 200 mg daily. Zestril demonstrated superior reductions of systolic and diastolic compared to hydrochlorothiazide in a population that was 75% Caucasian. Zestril was approximately equivalent to atenolol and metoprolol in reducing diastolic blood pressure, and had somewhat greater effects on systolic blood pressure.

Zestril had similar blood pressure reductions and adverse effects in younger and older (> 65 years) patients. It was less effective in reducing blood pressure in Blacks than in Caucasians.

In hemodynamic studies of Zestril in patients with essential hypertension, blood pressure reduction was accompanied by a reduction in peripheral arterial resistance with little or no change in cardiac output and in heart rate. In a study in nine hypertensive patients, following administration of Zestril, there was an increase in mean renal blood flow that was not significant. Data from several small studies are inconsistent with respect to the effect of lisinopril on glomerular filtration rate in hypertensive patients with normal renal function, but suggest that changes, if any, are not large.

In patients with renovascular hypertension Zestril has been shown to be well tolerated and effective in reducing blood pressure [see Warnings and Precautions (5.3) ].

Pediatric Patients: In a clinical study involving 115 hypertensive pediatric patients 6 to 16 years of age, patients who weighed < 50 kg received either 0.625 mg, 2.5 mg or 20 mg of Zestril once daily and patients who weighed ≥ 50 kg received either 1.25 mg, 5 mg, or 40 mg of Zestril once daily. At the end of 2 weeks, Zestril lowered trough blood pressure in a dose-dependent manner with antihypertensive efficacy demonstrated at doses > 1.25 mg (0.02 mg per kg). This effect was confirmed in a randomized withdrawal phase, where the diastolic pressure rose by about 9 mmHg more in patients randomized to placebo than compared to patients who remained on the middle and high doses of lisinopril. The dose-dependent antihypertensive effect of Zestril was consistent across several demographic subgroups: age, Tanner stage, gender, and race. In this study, lisinopril was generally well-tolerated.

In the above pediatric studies, Zestril was given either as tablets or in a suspension for those children and infants who were unable to swallow tablets or who required a lower dose than is available in tablet form [see Dosage and Administration (2.1) ].

14.2 Heart Failure

In two placebo controlled, 12-week clinical studies compared the addition of Zestril up to 20 mg daily to digitalis and diuretics alone. The combination of Zestril, digitalis and diuretics reduced the following signs and symptoms of heart failure: edema, rales, paroxysmal nocturnal dyspnea and jugular venous distention. In one of the studies, the combination of Zestril, digitalis and diuretics reduced orthopnea, presence of third heart sound and the number of patients classified as NYHA Class III and IV; and improved exercise tolerance. A large (over 3,000 patients) survival study, the ATLAS Trial, comparing 2.5 mg and 35 mg of lisinopril in patients with systolic heart failure, showed that the higher dose of lisinopril had outcomes at least as favorable as the lower dose.

During baseline-controlled clinical trials, in patients with systolic heart failure receiving digitalis and diuretics, single doses of Zestril resulted in decreases in pulmonary capillary wedge pressure, systemic vascular resistance and blood pressure accompanied by an increase in cardiac output and no change in heart rate.

14.3 Acute Myocardial Infarction

The Gruppo Italiano per lo Studio della Sopravvienza nell’Infarto Miocardico (GISSI-3) study was a multicenter, controlled, randomized, unblinded clinical trial conducted in 19,394 patients with acute myocardial infarction (MI) admitted to a coronary care unit. It was designed to examine the effects of short-term (6 week) treatment with lisinopril, nitrates, their combination, or no therapy on short-term (6 week) mortality and on long-term death and markedly impaired cardiac function. Hemodynamically- stable patients presenting within 24 hours of the onset of symptoms were randomized, in a 2 x 2 factorial design, to six weeks of either 1) Zestril alone (n=4841), 2) nitrates alone (n=4869), 3) Zestril plus nitrates (n=4841), or 4) open control (n=4843). All patients received routine therapies, including thrombolytics (72%), aspirin (84%), and a beta blocker (31%), as appropriate, normally utilized in acute myocardial infarction (MI) patients.

The protocol excluded patients with hypotension (systolic blood pressure ≤ 100 mmHg), severe heart failure, cardiogenic shock, and renal dysfunction (serum creatinine > 2 mg per dL and/or proteinuria > 500 mg per 24 h). Patients randomized to Zestril received 5 mg within 24 hours of the onset of symptoms, 5 mg after 24 hours, and then 10 mg daily thereafter. Patients with systolic blood pressure less than 120 mmHg at baseline received 2.5 mg of Zestril. If hypotension occurred, the Zestril dose was reduced or if severe hypotension occurred Zestril was stopped [see Dosage and Administration (2.3) ].

The primary outcomes of the trial were the overall mortality at 6 weeks and a combined end point at 6 months after the myocardial infarction, consisting of the number of patients who died, had late (day 4) clinical congestive heart failure, or had extensive left ventricular damage defined as ejection fraction ≤ 35% or an akinetic-dyskinetic [A-D] score ≥ 45%. Patients receiving Zestril (n=9646), alone or with nitrates, had an 11% lower risk of death (p = 0.04) compared to patients who did not receive Zestril (n=9672) (6.4% vs. 7.2%, respectively) at six weeks. Although patients randomized to receive Zestril for up to six weeks also fared numerically better on the combined end point at 6 months, the open nature of the assessment of heart failure, substantial loss to follow-up echocardiography, and substantial excess use of Zestril between 6 weeks and 6 months in the group randomized to 6 weeks of lisinopril, preclude any conclusion about this end point.

Patients with acute myocardial infarction, treated with Zestril, had a higher (9.0% versus 3.7%) incidence of persistent hypotension (systolic blood pressure < 90 mmHg for more than 1 hour) and renal dysfunction (2.4% versus 1.1%) in-hospital and at six weeks (increasing creatinine concentration to over 3 mg per dL or a doubling or more of the baseline serum creatinine concentration) [see Adverse Reactions (6.1) ].

16 HOW SUPPLIED/STORAGE AND HANDLING

Zestril is available as uncoated biconvex tablets in bottles of 90.

Strength | Color | Shape | Scored | Side 1/Side 2 | NDC 24979-
2.5 mg | White | Round | No | ZESTRIL 2½/135 | 238-07
5 mg | Pink | Capsule-Shaped | Yes | ZESTRIL/130 | 239-07
10 mg | Pink | Round | No | ZESTRIL 10/131 | 240-07
20 mg | Pale Brownish Red | Round | No | ZESTRIL 20/132 | 241-07
30 mg | Pale Brownish Red | Round | No | ZESTRIL 30/133 | 242-07
40 mg | Yellow | Round | No | ZESTRIL 40/134 | 243-07

Store at controlled room temperature, 20° to 25°C (68° to 77°F) [see USP]. Protect from moisture, freezing and excessive heat. Dispense in a tight container.

17 PATIENT COUNSELING INFORMATION

NOTE: This information is intended to aid in the safe and effective use of this medication. It is not a disclosure of all possible adverse or intended effects.

Pregnancy: Advise pregnant women and females of reproductive potential of the potential risk to a fetus. Advise females of reproductive potential to notify their healthcare provider with a known or suspected pregnancy [see Warnings and Precautions (5.1) and Use in Specific Populations (8.1)].

Angioedema: Angioedema, including laryngeal edema may occur at any time during treatment with angiotensin converting enzyme inhibitors, including Zestril. Tell patients to report immediately any signs or symptoms suggesting angioedema (swelling of face, extremities, eyes, lips, tongue, difficulty in swallowing or breathing) and to take no more drug until they have consulted with the prescribing physician.

Lactation: Advise women not to breastfeed during treatment with Zestril [see Use in Specific Populations (8.2)]

Symptomatic Hypotension: Tell patients to report light-headedness especially during the first few days of therapy. If actual syncope occurs, tell the patient to discontinue the drug until they have consulted with the prescribing physician.

Tell patients that excessive perspiration and dehydration may lead to an excessive fall in blood pressure because of reduction in fluid volume. Other causes of volume depletion such as vomiting or diarrhea may also lead to a fall in blood pressure; advise patients accordingly.

Hyperkalemia: Tell patients not to use salt substitutes containing potassium without consulting their physician.

Hypoglycemia: Tell diabetic patients treated with oral antidiabetic agents or insulin starting an ACE inhibitor to monitor for hypoglycaemia closely, especially during the first month of combined use [see Drug Interactions (7.2)].

Leukopenia/Neutropenia: Tell patients to report promptly any indication of infection (e.g., sore throat, fever), which may be a sign of leukopenia/neutropenia.

Zestril is a registered trademark of TWi Pharmaceuticals, Inc.

Distributed by:
UPSHER-SMITH LABORATORIES, LLC
Maple Grove, MN 55369

PKG03219

Revised 11/2024

PACKAGE LABEL

NDC 24979-238-07

Rx only

ONCE-DAILY
ZESTRIL®
(LISINOPRIL)

2.5 mg tablets

90 tablets

PACKAGE LABEL

NDC 24979-239-07

Rx only

ONCE-DAILY
ZESTRIL®
(LISINOPRIL)

5 mg tablets

90 tablets

PACKAGE LABEL

NDC 24979-240-07

Rx only

ONCE-DAILY
ZESTRIL®
(LISINOPRIL)

10 mg tablets
90 tablets

PACKAGE LABEL

NDC 24979-241-07

Rx only

ONCE-DAILY
ZESTRIL®
(LISINOPRIL)

20 mg tablets

90 tablets

PACKAGE LABEL

NDC 24979-242-07

Rx only

ONCE-DAILY
ZESTRIL®
(LISINOPRIL)

30 mg tablets
90 tablets

PACKAGE LABEL

NDC 24979-243-07

Rx only

ONCE-DAILY
ZESTRIL®
(LISINOPRIL)

40 mg tablets

90 tablets